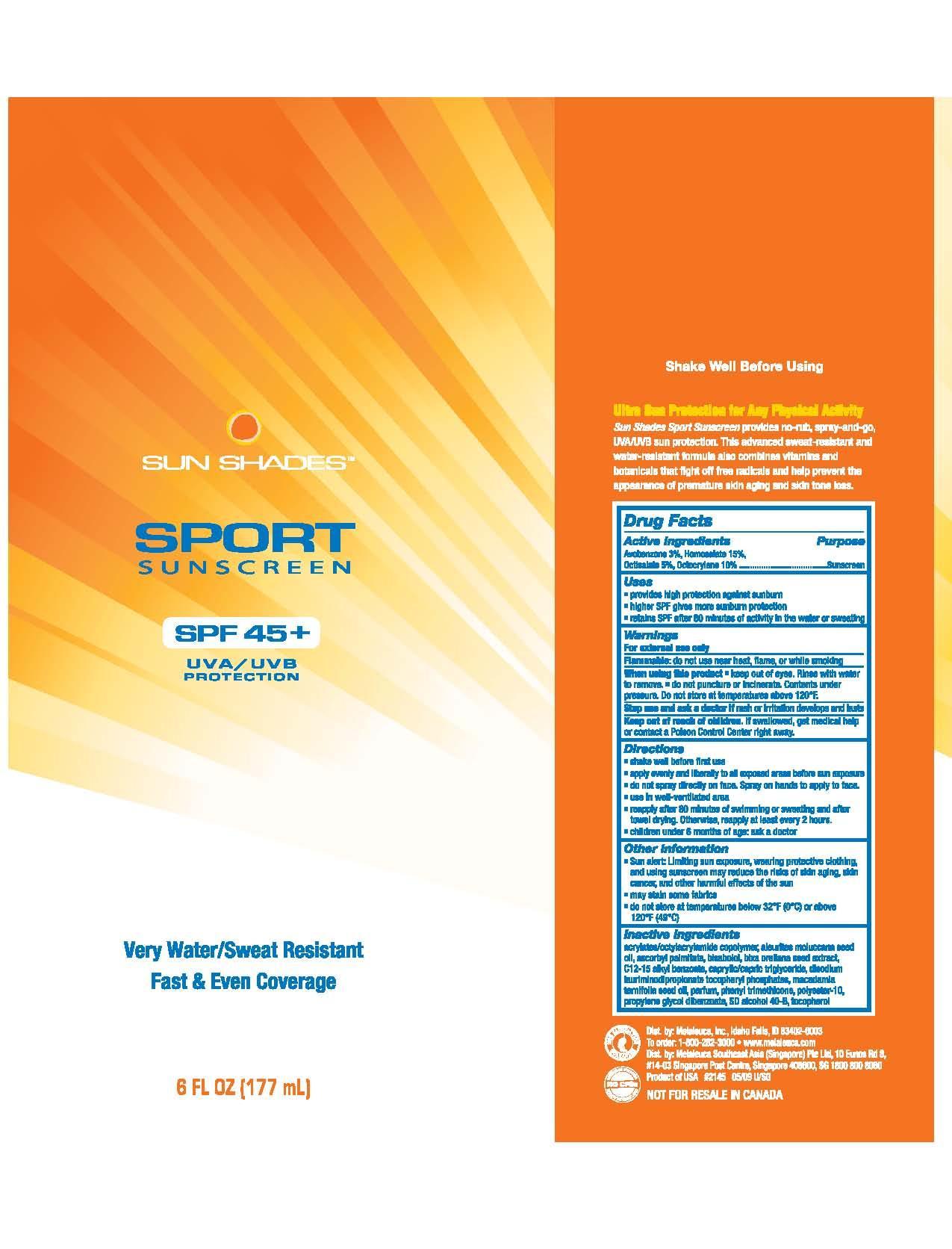 DRUG LABEL: Sun Shades
NDC: 54473-163 | Form: SPRAY
Manufacturer: Melaleuca, Inc.
Category: otc | Type: HUMAN OTC DRUG LABEL
Date: 20230111

ACTIVE INGREDIENTS: AVOBENZONE 4.7106 g/177 mL; HOMOSALATE 23.553 g/177 mL; OCTISALATE 7.851 g/177 mL; OCTOCRYLENE 15.702 g/177 mL
INACTIVE INGREDIENTS: ALCOHOL; ALPHA-TOCOPHEROL ACETATE; ASCORBYL PALMITATE; BIXA ORELLANA SEED; ALKYL (C12-15) BENZOATE; KUKUI NUT OIL; LEVOMENOL; MACADAMIA OIL; PHENYL TRIMETHICONE; PROPYLENE GLYCOL DIBENZOATE

Sun Shades Sport 45+

Active ingredients
Avobenzone 3%, Homosalate 15%, Octisalate 5%, Octocrylene 10%

Purpose
Sunscreen

Warnings
For external use only

Flammable: do not use near heat, flame, or while smoking

When using this product

- keep out of eyes. Rinse with water to remove.
- do not puncture or incinerate. Contents under pressure. Do not store at temperatures above 120°F.

Stop use and ask a doctor if rash or irritation develops and lasts

Keep out of reach of children. If swallowed, get medical help or contact a Poison Control Center right away.

Directions

- shake well before first use
- apply evenly and liberally to all exposed areas before sun exposure
- do not spray directly on face. Spray on hands to apply to face
- use in well-ventilated area
- reapply after 80 minutes of swimming or sweating and after towel drying. Otherwise, reapply at least every 2 hours.
- children under 6 months of age: ask a doctor

GENERAL PRECAUTIONS

- Sun alert: Limiting sun exposure, wearing protective clothing, and using sunscreen may reduce the risks of skin aging, skin cancer, and other harmful effects of the sun
- may stain some fabrics

Other information

- do not store at temperatures below 32°F (0°C) or above 120°F (49°C)

Inactive ingredients
acrylates/octacrylamide copolymer, aleurites moluccana seed oil, ascorbyl palmitate, bisabolol, bixa orellana seed extract, C12-15 alkyl benzoate, caprylic/capric triglyceride, disodium lauriminodipropionate tocopheryl phosphate, macadamia ternifolia seed oil, parfum, phenyl trimethicone, polyester-10, propylene glycol dibenzoate, SD alcohol 40-B, tocopherol